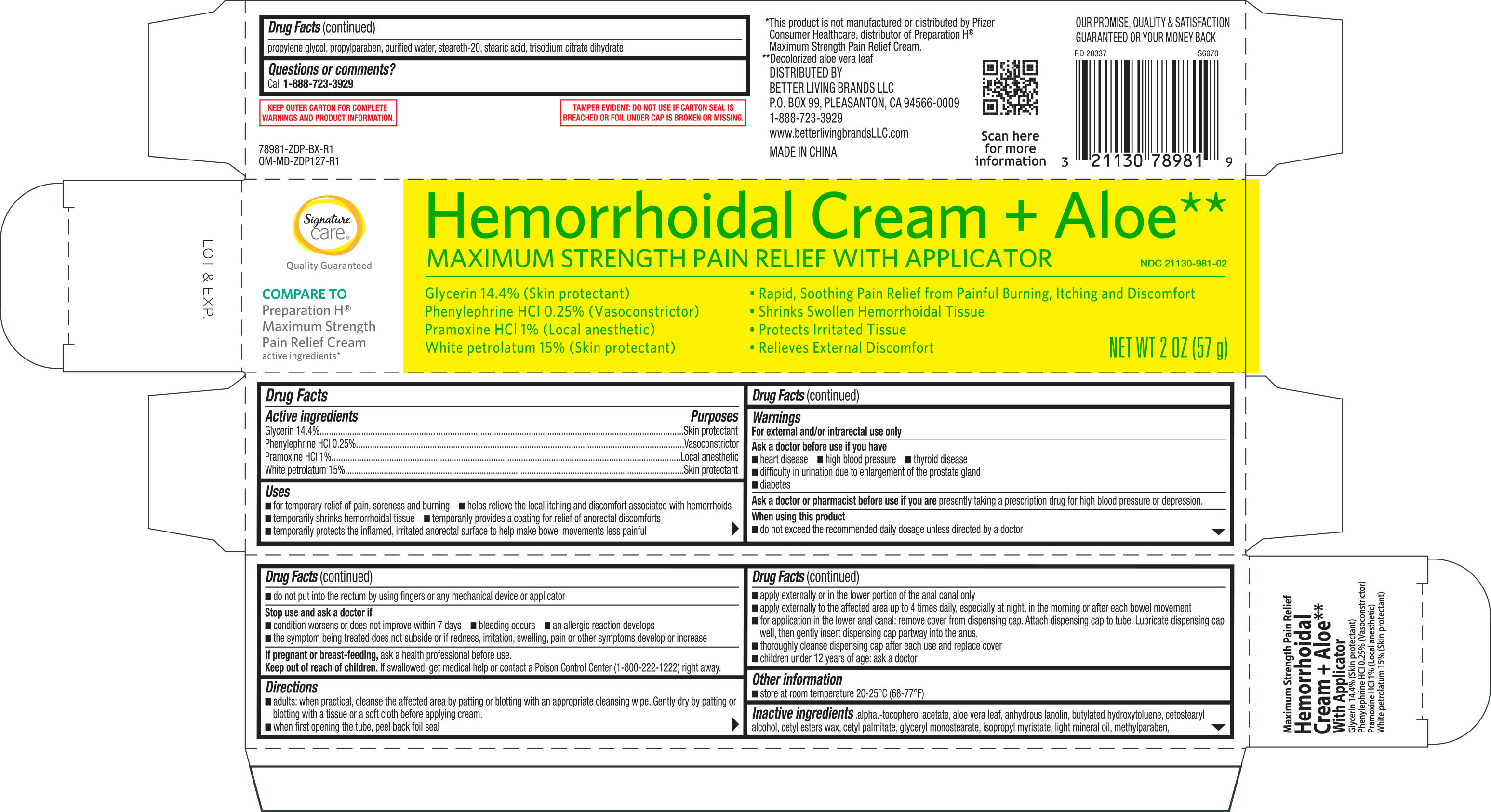 DRUG LABEL: Signature Care Hemorrhoidal Cream (with applicator)
NDC: 21130-981 | Form: CREAM
Manufacturer: BETTER LIVING BRANDS, LLC
Category: otc | Type: HUMAN OTC DRUG LABEL
Date: 20251024

ACTIVE INGREDIENTS: PHENYLEPHRINE HYDROCHLORIDE 2.5 mg/1 g; PRAMOXINE HYDROCHLORIDE 10 mg/1 g; GLYCERIN 144 mg/1 g; PETROLATUM 150 mg/1 g
INACTIVE INGREDIENTS: STEARETH-20; PROPYLENE GLYCOL; METHYLPARABEN; PROPYLPARABEN; BUTYLATED HYDROXYTOLUENE; WATER; CETYL PALMITATE; CETYL ESTERS WAX; STEARIC ACID; .ALPHA.-TOCOPHEROL ACETATE; ALOE VERA LEAF; LANOLIN; GLYCERYL MONOSTEARATE; TRISODIUM CITRATE DIHYDRATE; ISOPROPYL MYRISTATE; CETOSTEARYL ALCOHOL; LIGHT MINERAL OIL

Signature Care Hemorrhoidal Cream + Aloe Max. Strength Pain Relief w/Applicator 2 oz ZDP 78981

Active ingredients Purpose

Glycerin 14.4%............................................................Skin protectant

Phenylephrine HCl 0.25%...........................................Vasconstrictor

Pramoxine HCl 1%......................................................Local anesthetic

White petrolatum 15%.................................................Skin protectant

Uses

- for temporary relief of pain, soreness and burning
- helps relieve the local itching and discomfort associated with hemorrhoids
- temporarily shrinks hemorrhoidal tissue
- temporarily provides a coating for relief of anorectal discomforts
- temporarily protects the inflamed, irritated anorectal surface to make bowel movements less painful

Warnings

For external and/or intrarectal use only

Ask a doctor before use if you have

- heart disease
- high blood pressure
- thyroid disease
- difficult in urination due to enlargement of the prostate gland
- diabetes

When using this product

- do not exceed the recommended daily dosage unless directed by a doctor
- do not put into the rectum by using fingers or any mechanical device or applicator

Stop use and ask a doctor if

- condition worsens or does not improve within 7 days
- bleeding occurs
- an allergic reaction develops
- the symptom being treated does not subside or if redness, irritation, swelling, pain or other symptoms develop or increase

PREGNANCY OR BREAST FEEDING

If pregnant or breast-feeding, ask a health professional before use.

Keep out of reach of children. If swallowed, get medical help or contact a Poison Control Center (1-800-222-1222) right away.

Directions

- adults: when practical, cleanse the affected area by patting or blotting with an appropriate cleansing wipe. Gently dry by patting or blotting with a tissue or a soft cloth before applying cream.
- when first opening the tube, peel back foil seal
- apply externally or in the lower portion of the anal canal only
- apply externally to the affected area up to 4 times daily, especially at night, in the morning or after each bowel movement
- for application in the lower anal canal: remove cover from dispensing cap. Attach dispensing cap to tube. Lubricate dispensing cap well, then gently insert dispensing cap partway into the anus
- thoroughly cleanse dispensing cap after each use and replace cover
- children under 12 years of age: ask a doctor

Other information

- store at room temperature 20-25°C (68-77°F)

Inactive ingredients

.alpha.-tocopherol acetate, aloe vera leaf, anhydrous lanolin, butylated hydroxytoluene, cetostearyl alcohol, cetyl esters wax, cetyl palmitate, glycryl monostearate, isopropyl myristate, light mineral oil, methylparaben, propylene glycol, propylparaben, purified water, steareth-20, stearic acid, trisodium citrate dihydrate

DOSAGE AND ADMINISTRATION

Distributed by:

Better Living Brands LLC

Made in China